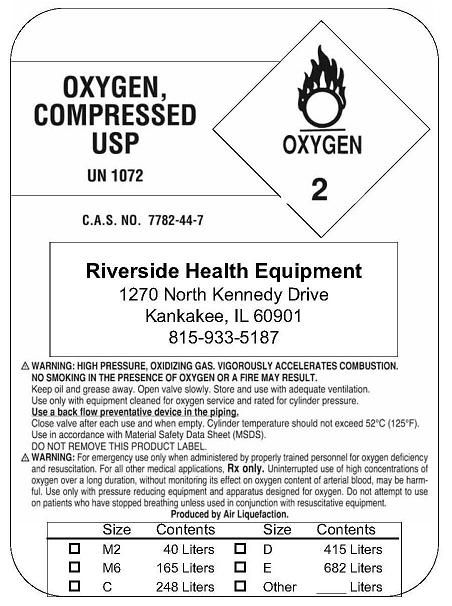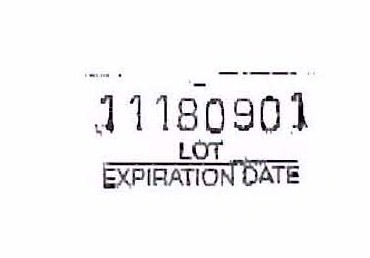 DRUG LABEL: Oxygen
NDC: 66966-0001 | Form: GAS
Manufacturer: Riverside Health Equipment
Category: prescription | Type: HUMAN PRESCRIPTION DRUG LABEL
Date: 20091223

ACTIVE INGREDIENTS: Oxygen 99 L/100 L

Oxygen